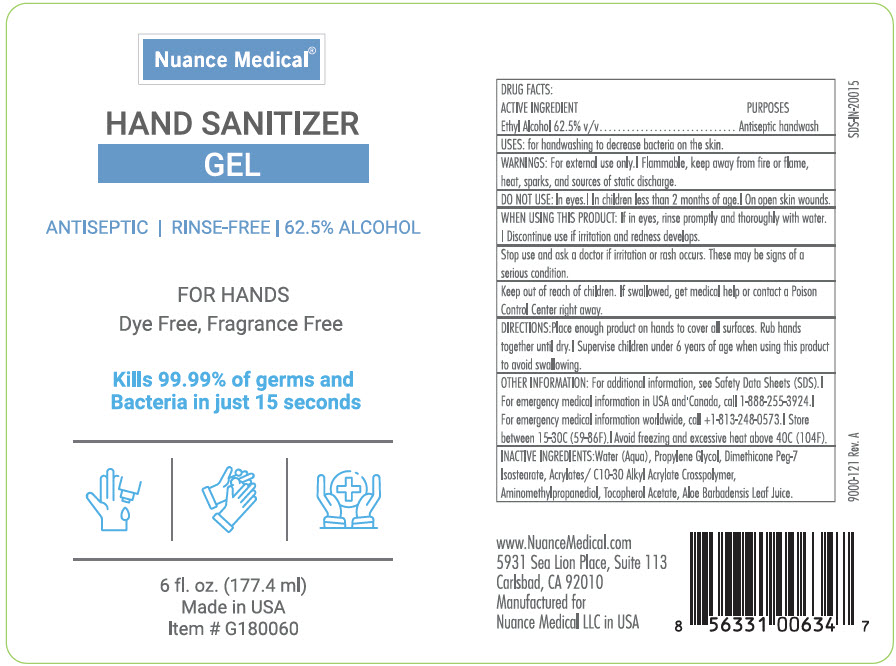 DRUG LABEL: Hand Sanitizer
NDC: 74318-100 | Form: GEL
Manufacturer: Nuance Medical, LLC
Category: otc | Type: HUMAN OTC DRUG LABEL
Date: 20210714

ACTIVE INGREDIENTS: ALCOHOL 62.5 mL/100 mL
INACTIVE INGREDIENTS: Water; Propylene Glycol; AMINOMETHYLPROPANOL; DIMETHICONE PEG-8 ISOSTEARATE; CARBOMER INTERPOLYMER TYPE A (ALLYL SUCROSE CROSSLINKED); Tocopherol; Aloe Vera Leaf

Hand Sanitizer

Drug Facts

Active ingredient

Ethyl Alcohol 62.5% v/v

Purposes

Antiseptic handwash

Uses

for handwashing to decrease bacteria on the skin

Warnings

- For external use only
- Flammable, keep away from fire or flame, heat, sparks, and sources of static discharge

Do not use

- In eyes| In children less than 2 months of ag| on open skin wounds

When using this product

- If in eyes, rinse promptly and thoroughly with water
- Discontinue use if irritation and redness develops

Stop use and ask a doctor if skin irritation or redness occurs or persists for more than 72 hours.

Keep out of reach of children. If swallowed, get medical help or contact a Poison Control Center right away.

Directions

Place enough product on hands to cover all surfaces. Rub hands together until dry. Supervise children 6 years of age when using this product to avoid swallowing

Other Information

- For additional information, see Safety Data Sheets (SDS)
- For emergency medical information in USA and Canada, call 1-888-255-3924
- For emergency medical information worldwide, call 1-813-248-0573
- Store between 15-30C (59-86F) | Avoid freezing and excessive heat above 40C (104F)

Inactive Ingredients

water (aqua), propylene glycol, dimethicone PEG-7 Isostearate, acrylates/ C10-30 Alkyl Acrylate Crosspolymer, aminomethylpropanediol, tocopherol acetate, aloe barbadensis leaf juice

PRINCIPAL DISPLAY PANEL - 177.4 ml Bottle Label

Nuance Medical®

HAND SANITIZER
GEL

ANTISEPTIC | RINSE-FREE | 62.5% ALCOHOL

FOR HANDS
Dye Free, Fragrance Free

Kills 99.99% of germs and
Bacteria in just 15 seconds

6 fl. oz. (177.4 ml)

Made in USA

Item # G180060